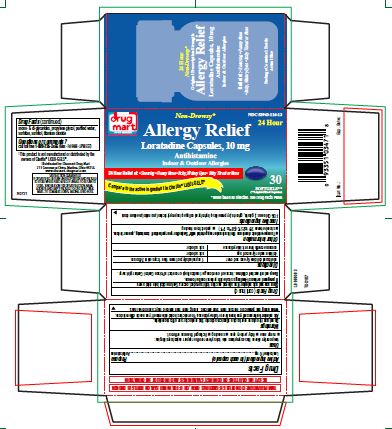 DRUG LABEL: Allergy Relief
NDC: 53943-116 | Form: CAPSULE, LIQUID FILLED
Manufacturer: DISCOUNT DRUG MART, INC.
Category: otc | Type: HUMAN OTC DRUG LABEL
Date: 20221230

ACTIVE INGREDIENTS: LORATADINE 10 mg/1 1
INACTIVE INGREDIENTS: CAPRYLIC/CAPRIC MONO/DI-GLYCERIDES; FD&C BLUE NO. 1; GELATIN; GLYCERIN; HYPROMELLOSES; HYDROLYSED BOVINE COLLAGEN (ENZYMATIC; 2000-5000 MW); ISOPROPYL ALCOHOL; MANNITOL; PROPYLENE GLYCOL; WATER; SORBITAN; SORBITOL; TITANIUM DIOXIDE

Drug Facts

Active ingredient (in each capsule)

Loratadine 10 mg

Purpose

Antihistamine

Uses

temporarily relieves these symptoms due to hay fever or other upper respiratory allergies:

- runny nose
- itchy, watery eyes
- sneezing
- itching of the nose or throat

Warnings

Do not use

if you have ever had an allergic reaction to this product or any of its ingredients.

Ask a doctor before use if you have

liver or kidney disease. Your doctor should determine if you need a different dose.

When using this product

do not take more than directed. Taking more than directed may cause drowsiness.

Stop use and ask a doctor if

an allergic reaction to this product occurs. Seek medical help right away.

If pregnant or breast-feeding,

ask a health professional before use.

Keep out of reach of children.

In case of overdose, get medical help or contact a Poison Control Center right away.

Directions

adults and children 6 years and over | 1 capsule daily; not more than 1 capsule in 24 hours
children under 6 years of age | ask a doctor
consumers with liver or kidney disease | ask a doctor

Other information

- Safety sealed: do not use if individual blister unit printed with Loratadine Capsule, 10 mg is open or torn.
- store between 20° to 25°C (68° to 77°F)
- protect from freezing

Inactive ingredients

FD&C blue no.1, gelatin, glycerin, hypromellose, hydrolyzed collagen, isopropyl alcohol, mannitol, medium chain mono- & di-glycerides, propylene glycol, purified water, sorbitan, sorbitol, titanium dioxide

Questions or comments?

call toll free 1-888-235-2466 (Mon - Fri 9AM - 5PM EST)

TAMPER EVIDENT: DO NOT USE IF CARTON IS OPEN, OR IF FOIL INNER SEAL ON BOTTLE IS BROKEN

KEEP THIS CARTON FOR COMPLETE WARNINGS AND PRODUCT INFORMATION

†This product is not manufactured or distributed by the owners of Claritin® LIQUI-GELS®.

Distributed by: Discount Drug Mart
211 Commerce Drive, Medina, Ohio 44256
www.discount-drugmart.com

SATISFACTION GUARANTEED
IF DISSATISFIED, RETURN UNUSED PORTION AND PACKAGE
TO STORE WHERE PURCHASED. IF UNABLE TO RETURN TO
STORE, SEND REASON FOR DISSATISFACTION, NAME,
ADDRESS AND EMPTY PACKAGE TO: DISCOUNT DRUG
MART, 211 COMMERCE DRIVE, MEDINA, OHIO 44256

R0721

Principal Display Panel

DISCOUNT

drug

mart

FOOD MARKET

AN EMPLOYEE OWNERSHIP COMPANY

Non-Drowsy*

NDC 53943-116-13

24 Hour

Allergy Relief

Loratadine Capsules, 10 mg

Antihistamine

Indoor & Outdoor Allergies

24 Hour Relief of: • Sneezing • Runny Nose • Itchy, Watery Eyes • Itchy Throat or Nose

†Compare to the active ingredient in Claritin® LIQUI-GELS®

30

SOFTGELS**

(**Liquid-Filled Capsules)

*When taken as directed. See Drug Facts Panel.